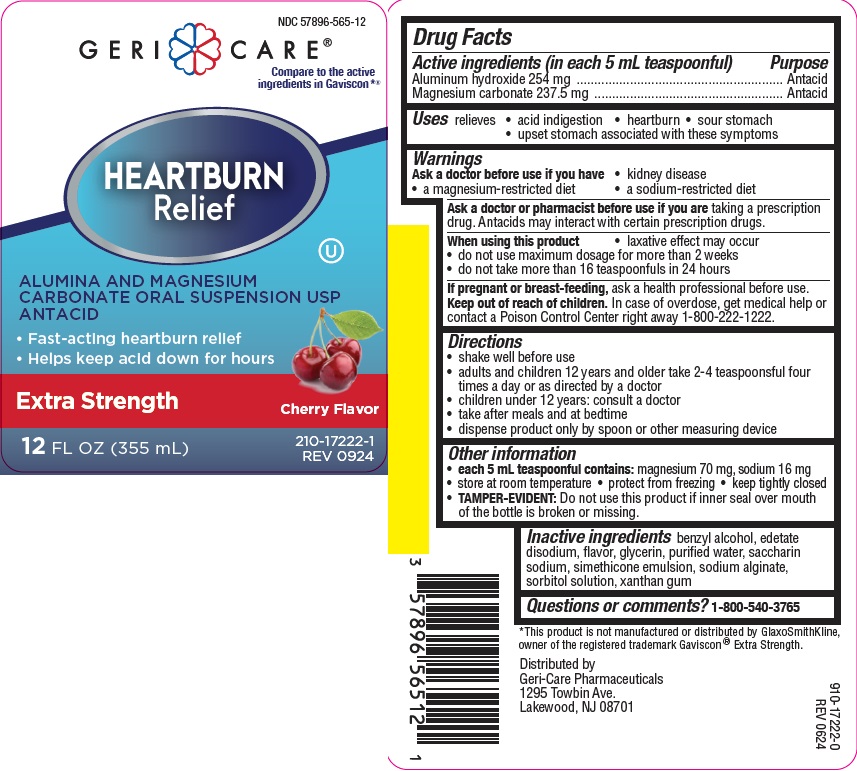 DRUG LABEL: HEARTBURN RELIEF
NDC: 57896-565 | Form: SUSPENSION
Manufacturer: GERI-CARE PHARMACEUTICALS, CORP
Category: otc | Type: HUMAN OTC DRUG LABEL
Date: 20241209

ACTIVE INGREDIENTS: ALUMINUM HYDROXIDE 254 mg/5 mL; MAGNESIUM CARBONATE 237.5 mg/5 mL
INACTIVE INGREDIENTS: BENZYL ALCOHOL; EDETATE DISODIUM; GLYCERIN; WATER; SACCHARIN SODIUM; SODIUM ALGINATE; SORBITOL; XANTHAN GUM; DIMETHICONE

gc ES heartburn relief 565

Active ingredients (in each 5 mL teaspoonful)

Aluminum hydroxide 254 mg
Magnesium carbonate 237.5 mg

Purpose

Antacid

Uses

relieves

- heartburn
- sour stomach
- acid indigestion
- upset stomach associated with these symptoms

Warnings

Ask a doctor before use if you have

- kidney disease
- a magnesium-restricted diet
- a sodium-restricted diet

Ask a doctor or pharmacist before use if you are taking a prescription drug. Antacids may interact with certain prescription drugs.

When using this product

- laxative effect may occur
- do not use maximum dosage for more than 2 weeks
- do not take more than 16 teaspoonfuls in 24 hours

If pregnant or breast-feeding, ask a health professional before use.

Keep out of reach of children.In case of overdose, get medical help or
contact a Poison Control Center (1-800-222-1222) right away.

Directions

- shake well before use
- adults and children 12 years and older take 2-4 teaspoonsful four times a day or as directed by a doctor
- children under 12 years: consult a doctor
- take after meals and at bedtime
- dispense product only by spoon or other measuring device

Other information

- each 5 mL teaspoonful contains: magnesium 70 mg, sodium 16 mg
- store at room temperature
- protect from freezing
- keep tightly closed
- TAMPER-EVIDENT: Do not use this product if inner foil seal over mouth of the bottle is broken or missing.

Inactive ingredients

benzyl alcohol, edetate disodium, flavor, glycerin, purified water, saccharin sodium, simethicone emulsion, sodium alginate, sorbitol solution, xanthan gum

Questions or comments?

1-800-540-3765